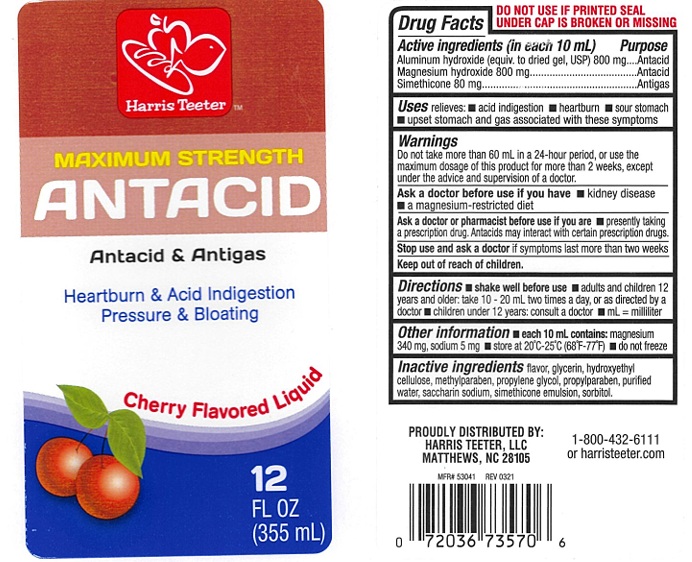 DRUG LABEL: Maximum Strength Antacid Cherry
NDC: 69256-508 | Form: LIQUID
Manufacturer: Harris Teeter, LLC
Category: otc | Type: Human OTC Drug Label
Date: 20250212

ACTIVE INGREDIENTS: ALUMINUM HYDROXIDE 800 mg/10 mL; MAGNESIUM HYDROXIDE 800 mg/10 mL; DIMETHICONE 80 mg/10 mL
INACTIVE INGREDIENTS: GLYCERIN; HYDROXYETHYL CELLULOSE, UNSPECIFIED; METHYLPARABEN; PROPYLENE GLYCOL; PROPYLPARABEN; WATER; SACCHARIN SODIUM; SORBITOL

Maximum strength Antacid Cherry liquid

ACTIVE INGREDIENTS (in each 10 mL)

Aluminum hydroxide (equiv. to dried gel, USP) 800 mg
Magnesium hydroxide 800 mg
Simethicone 80 mg

PURPOSE

Antacid
Antacid
Antigas

USE(S)

relieves:

- acid indigestion
- heartburn
- sour stomach
- upset stomach and gas associated with these symptoms

WARNINGS

Do not take more than 60 mL in a 24-hour period, or use the maximum dosage of this product for more than 2 weeks, except under the advice and supervision of a doctor.

ASK A DOCTOR BEFORE USE IF YOU HAVE

- kidney disease
- a magnesium-restricted diet

ASK A DOCTOR OR PHARMACIST BEFORE USE IF YOU ARE

- presently taking a prescription drug. Antacids may interact with certain prescription drugs.

STOP USE AND ASK DOCTOR

if symptoms last more than two weeks

KEEP OUT OF REACH OF CHILDREN

.

DIRECTIONS

- shake well before use
- adults and children 12 years and older: take 10 mL to 20 mL two times a day, or as directed by a doctor
- children under 12 years: consult a doctor
- mL = milliliter

OTHER INFORMATION

- each 10 mL contains: magnesium 340 mg, sodium 5 mg
- store at 20ºC-25ºC (68º-77ºF)
- do not freeze

INACTIVE INGREDIENTS

flavor, glycerin, hydroxyethyl cellulose, methylparaben, propylene glycol, propylparaben, purified water, saccharin sodium, simethicone emulsion, sorbitol

PRINCIPAL DISPLAY PANEL

Harris Teeter™
NDC 69256-508-05
MAXIMUM STRENGTH
Antacid

Antacid & Antigas

Heartburn & Acid Indigestion

Pressure & Bloating

Cherry Flavored Liquid

12 FL OZ (355 mL)